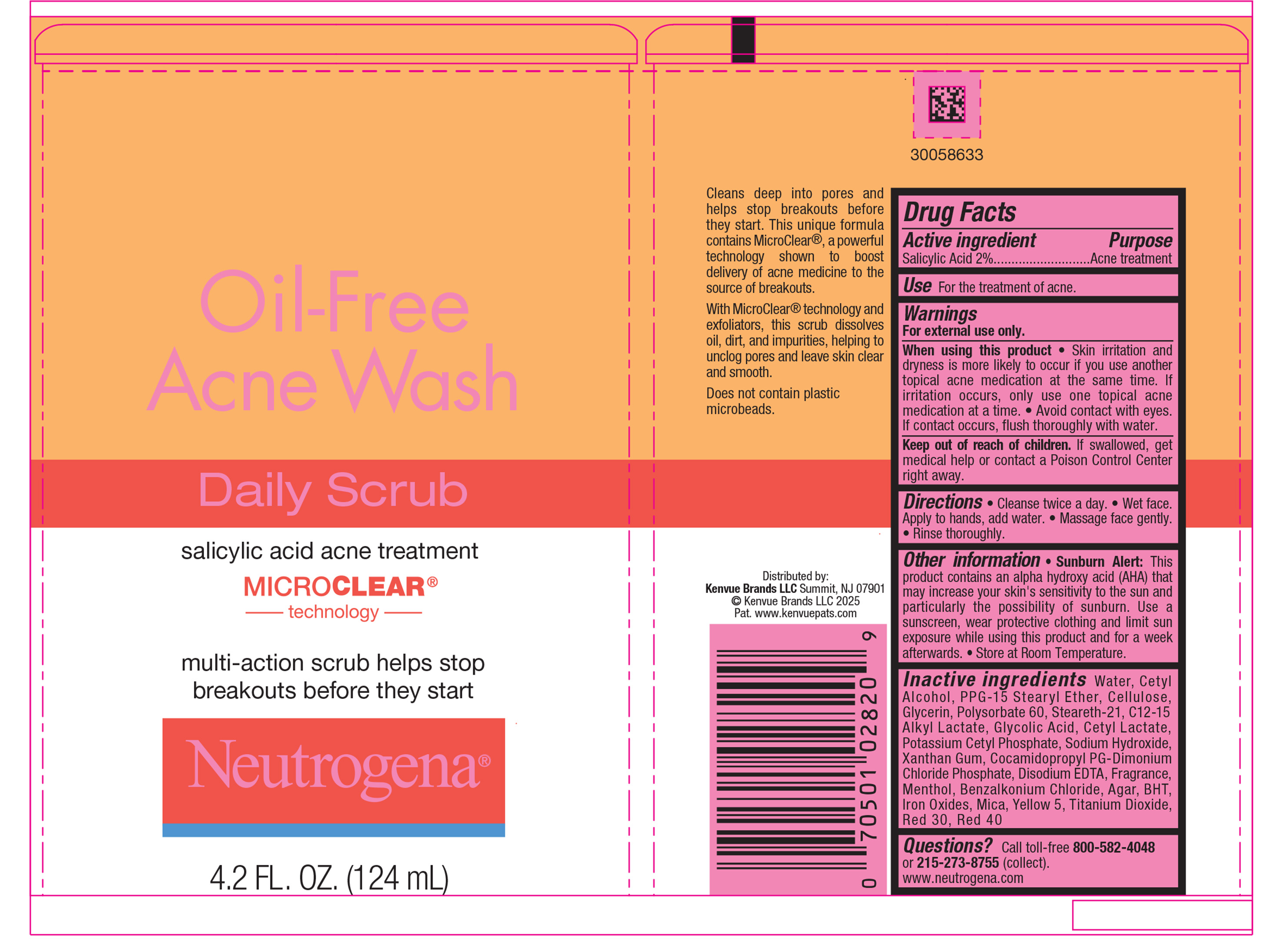 DRUG LABEL: Neutrogena Oil-Free Acne Wash Daily Scrub
NDC: 69968-0908 | Form: LIQUID
Manufacturer: Kenvue Brands LLC
Category: otc | Type: HUMAN OTC DRUG LABEL
Date: 20250820

ACTIVE INGREDIENTS: SALICYLIC ACID 20 mg/1 mL
INACTIVE INGREDIENTS: PPG-15 STEARYL ETHER; POLYSORBATE 60; STEARETH-21; C12-15 ALKYL LACTATE; GLYCOLIC ACID; COCAMIDOPROPYL PG-DIMONIUM CHLORIDE PHOSPHATE; BENZALKONIUM CHLORIDE; TITANIUM DIOXIDE; RED 30; RED 40; POTASSIUM CETYL PHOSPHATE; EDETATE DISODIUM; FERROUS OXIDE; XANTHAN GUM; GLYCERIN; WATER; CETYL LACTATE; AGAR; BHT; MICA; CETYL ALCOHOL; POWDERED CELLULOSE; YELLOW 5; SODIUM HYDROXIDE; MENTHOL

Neutrogena Oil-Free Acne Wash Daily Scrub

Drug Facts

Active ingredient

Salicylic Acid 2%

Purpose

Acne treatment

Use

For the treatment of acne

Warnings

For external use only.

▪ When using this product

▪ Skin irritation and dryness is more likely to occur if you use another topical acne medication at the same time. If irritation occurs, only use one topical acne medication at a time.

▪ Avoid contact with eyes. If contact occurs, flush thoroughly with water.

▪ Keep out of reach of children. If swallowed, get medical help or contact a Poison Control Center right away.

Directions

▪ Cleanse twice a day.

▪ Wet face. Apply to hands, add water

▪ Massage face gently.

▪ Rinse thoroughly.

Other information

• Sunburn Alert: This product contains an alpha hydroxy acid (AHA) that may increase your skin’s sensitivity to the sun and particularly the possibility of sunburn. Use a sunscreen, wear protective clothing and limit sun exposure while using this product and for a week afterwards. • Store at Room Temperature.

Inactive ingredients

Water, Cetyl Alcohol, PPG-15 Stearyl Ether, Cellulose, Glycerin, Polysorbate 60, Steareth-21, C12-15 Alkyl Lactate, Glycolic Acid, Cetyl Lactate, Potassium Cetyl Phosphate, Sodium Hydroxide, Xanthan Gum, Cocamidopropyl PG-Dimonium Chloride Phosphate, Disodium EDTA, Fragrance, Menthol, Benzalkonium Chloride, Agar, BHT, Iron Oxides, Mica, Yellow 5, Titanium Dioxide, Red 30, Red 40

Questions?

Call toll-free 800-582-4048 or 215-273-8755 (collect). www.neutrogena.com

Distributed by:
Kenvue brands LLC

Summit, NJ 07901

PRINCIPAL DISPLAY PANEL - 124 mL Tube Label

Oil-Free

Acne Wash

Daily Scrub

salicylic acid acne treatment

MICRO CLEAR®

technology

multi-action scrub helps stop

breakouts before they start

Neutrogena®

4.2 FL.OZ. (124mL)